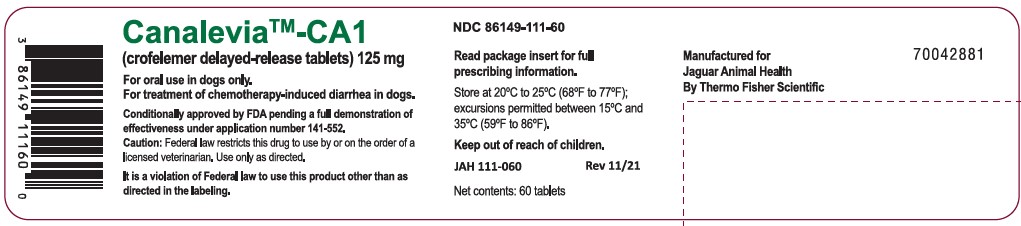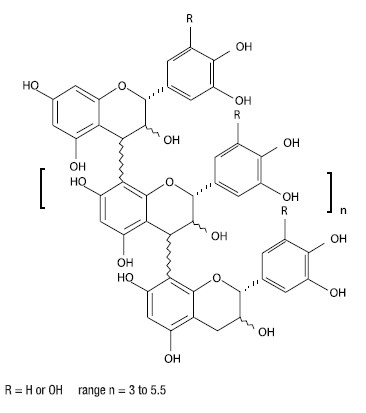 DRUG LABEL: CANALEVIA-CA1
NDC: 86149-111 | Form: TABLET, DELAYED RELEASE
Manufacturer: Jaguar Animal Health
Category: animal | Type: PRESCRIPTION ANIMAL DRUG LABEL
Date: 20260223

ACTIVE INGREDIENTS: CROFELEMER 125 mg/1 1
INACTIVE INGREDIENTS: CELLULOSE, MICROCRYSTALLINE; CROSCARMELLOSE SODIUM; SILICON DIOXIDE; MAGNESIUM STEARATE; ETHYL ACRYLATE; TALC; TRIETHYL CITRATE; XANTHAN GUM; TITANIUM DIOXIDE; PROPYLPARABEN; METHYLPARABEN

CANALEVIA™-CA1
(crofelemer delayed-release tablets)
125 mg

antidiarrheal

For oral use in dogs only

CAUTION: Federal (USA) law restricts this drug to use by or on the order of a licensed veterinarian. Use only as directed. It is a violation of Federal Law to use this product other than as directed in the labeling.

Conditionally approved by FDA pending a full demonstration of effectiveness under application number 141-552.

DESCRIPTION:

CANALEVIA-CA1 (crofelemer delayed-release tablets) is an antidiarrheal, enteric-coated drug product for oral administration. CANALEVIA-CA1 containing 125 mg of crofelemer, a botanical drug substance that is derived from the red latex of Croton lechleri Müll. Arg. Crofelemer is an oligomeric proanthocyanidin mixture primarily composed of (+)–catechin, (–)–epicatechin, (+)–gallocatechin, and (–)–epigallocatechin monomer units linked in random sequence, as represented below. The average degree of polymerization for the oligomers ranges between 5 and 7.5, as determined by phloroglucinol degradation.

INDICATION:

CANALEVIA-CA1 is indicated for the treatment of chemotherapy-induced diarrhea in dogs.

DOSAGE AND ADMINISTRATION:

Administer 1 tablet orally twice daily for 3 days for dogs weighing ≤ 140 pounds. Administer 2 tablets orally twice daily for 3 days for dogs weighing >140 pounds. Tablets should not be broken, crushed, or chewed. If the tablet is chewed, one additional dose may be administered. Give with or without food.

CONTRAINDICATIONS:

Do not use in patients with a known hypersensitivity to crofelemer.

WARNINGS:

Not for use in humans. Keep this and all medications out of reach of children. Consult a physician in case of accidental ingestion by humans.

Keep CANALEVIA-CA1 in a secure location out of reach of dogs, cats, and other animals to prevent accidental ingestion or overdose.

PRECAUTIONS:

The safe use of CANALEVIA-CA1 has not been evaluated in dogs that are pregnant, lactating, or intended for breeding.

Prior to using CANALEVIA-CA1, rule out infectious etiologies of diarrhea. Prescribing CANALEVIA-CA1 to dogs with diarrhea secondary to infectious etiologies may delay appropriate treatment.

ADVERSE REACTIONS:

In a masked, randomized study to support a reasonable expectation of effectiveness (CANA-001a) there was similar incidence of adverse events in dogs administered Crofelemer (not commercial formulation) compared to control dogs administered a vehicle control. Crofelemer was administered orally twice a day for three days as enteric-coated beads containing 40 mg of the active ingredient. The vehicle control was enteric-coated beads without the active ingredient. The dogs had daily assessments for changes in attitude, hydration, appetite, and abdominal palpation. Table 1 shows the adverse reactions during CANA-001a study.

Table 1. Adverse Reactions in CANA-001a Study to Support Reasonable Expectation of Effectiveness

Adverse Reaction^1 | Crofelemer; N = 29 | Vehicle Control; N = 32
Appetite decreased | 7 (24%) | 9 (28%)
Attitude depressed | 5 (17%) | 5 (16%)
Activity decreased | 4 (14%) | 4 (13%)
Dehydration^2 | 4 (14%) | 5 (16%)
Abdominal palpation indicated pain^3 | 3 (10%) | 5 (16%)
Vomiting | 1 (3%) | 2 (6%)

^1 Dogs may have experienced more than one occurrence and more than one type of abnormal assessment during the study

^2 Two crofelemer treated dogs and one vehicle control dog were administered fluid therapy

^3 One of the vehicle control dogs was reported to not allow abdominal palpation at one timepoint on Day 2

In an open-label pilot study (CANA-001b) 48 dogs were administered crofelemer (not commercial formulation) orally twice a day for three days. The adverse reactions included decreased appetite in 16/48 (33%) dogs, vomiting in 3 (6%) dogs, decreased activity in 3 dogs (6%), abdominal pain in 1 (2%) dog, and 1 (2%) dog had blood in feces.

In a separate pilot clinical field study (CANA-003), dogs with acute diarrhea were randomized to receive crofelemer or placebo tablets. The study included 22 dogs administered crofelemer (not commercial formulation) tablets and 112 dogs administered 125 mg CANALEVIA-CA1 tablets. There were 66 dogs who received placebo tablets. Dogs were administered tablets orally twice a day for three days. Hematology and clinical chemistry were obtained prior to dosing and on Day 3 at the end of the study. Table 2 shows adverse reactions during the study.

Table 2. Adverse Reactions in Pilot Field Study CANA-003

Adverse Reaction | Crofelemer; N=134 | Placebo; N=66
Vomiting | 11 (8%) | 1 (2%)
Decreased blood glucose^1 | 10 (8%) | 3 (5%)
Urinary system abnormality^2 | 10 (8%) | 2 (3%)
Upper respiratory signs^3 | 7 (5%) | 0 (0%)
Decreased blood calcium^4 | 5 (4%) | 0 (0%)

^1 Dogs with decreased blood glucose at study end had normal blood glucose (reference range 74-145 mg/dL) prior to dosing. None of the dogs were reported to be clinically affected by the decreased blood glucose. The low blood glucose values ranged from 34 to 71 mg/dL.

^2 Urinary system abnormalities were documented as development of a urinary tract infection, cystitis, or a worsening pyuria in the urine.

^3 Upper respiratory signs included coughing, nasal discharge, sneezing, and congestion.

^4 Dogs with decreased serum calcium (reference range 8.7-12 mg/dL) at study end had normal calcium at screening. The decreased calcium values were not associated with decreased albumin values. None of the dogs were reported to be clinically affected by the decreased serum calcium. The lowest reported calcium was 5.8 mg/dL.

Five dogs administered crofelemer and one placebo group dog were removed from the study for no improvement in stools. One additional dog administered crofelemer was removed for hemorrhagic stool.

CONTACT INFORMATION: To report suspected adverse drug events and/or to obtain a copy of the Safety Data Sheet (SDS) or for technical assistance, call Jaguar Animal Health at 1-877-787-3001. For additional information about adverse drug experience reporting for animal drugs, contact FDA at 1-888-FDA-VETS or http://www.fda.gov/reportanimalae.

CLINICAL PHARMACOLOGY:

Mechanism of Action: In humans, crofelemer is an inhibitor of both the cyclic adenosine monophosphate (cAMP)-stimulated cystic fibrosis transmembrane conductance regulator (CFTR) chloride ion (Cl-) channel, and the calcium-activated Cl- channels (CaCC) at the luminal membrane of enterocytes. The CFTR Cl- channel and CaCC regulate Cl- and the osmotic gradient which causes fluid influx into the lumen. Crofelemer inhibits the hypersecretion of Cl- in diarrhea and normalizes the fluid influx into the GI tract. The mechanism of action in the dog has not been fully characterized.

REASONABLE EXPECTATION OF EFFECTIVENESS:

A reasonable expectation of effectiveness may be demonstrated based on evidence such as, but not limited to, pilot data in the target species or studies from published literature.

CANALEVIA-CA1 is conditionally approved pending a full demonstration of effectiveness.

Additional information for Conditional Approvals can be found at www.fda.gov/animalca.

A reasonable expectation of effectiveness for CANALEVIA-CA1 is based on a pilot field study.

A multi-site, randomized, masked, vehicle-controlled field study in dogs with diarrhea of various etiologies was conducted to assess the effectiveness of crofelemer (not commercial formulation). The effectiveness dataset included 12 dogs administered crofelemer and 12 dogs administered vehicle control. Dogs were between the ages of four months and 12 years with a fecal score of 4 or 5 (watery or liquid stools with little or no particulate matter or severe watery diarrhea with no particulate matter visible). Crofelemer was administered at a dose of 1.9 to 12.9 mg/kg every 12 hours for three days. Fecal scores were obtained every four hours during the three day study. Fecal scores were based on a modified version of the Purina Fecal Scoring System and were defined as:

1. Well-formed stools with slightly moist surface which leaves marks when picked up

2. Soft or very soft, moist, amorphous

3. Viscous liquid with some particulate matter

4. Watery, liquid stools with little particulate matter visible

5. Severe watery diarrhea, no particulate matter visible

6. Hemorrhagic diarrhea

The resolution of diarrhea was considered treatment success and was defined as a fecal score of 1 or 2. After a dog achieved resolution of diarrhea during the 3 day study, subsequent fecal scores had to be maintained as a 1 or 2 in order to be considered a treatment success. The resolution of diarrhea per day (24 hour treatment block) is described in Table 3.

Table 3. Number of Dogs Achieving Resolution of Diarrhea per 24 Hour Treatment Block

Treatment block | Crofelemer; N=12 | Vehicle Control; N=12
≤24 hours | 2 (17%) | 0 (0%)
>24 hours and ≤48 hours | 2 (17%) | 0 (0%)
>48 hours and ≤72 hours | 5 (42%) | 3 (25%)

Daily assessments included body temperature; fecal scores; and a scored assessment of general attitude, hydration status, appetite, and reaction to abdominal palpation (see ADVERSE REACTIONS).

TARGET ANIMAL SAFETY:

The safety of CANALEVIA-CA1 and crofelemer was evaluated in four laboratory studies.

Target Animal Safety Study: In a 9 day laboratory safety study, healthy four month old Beagle dogs were orally administered crofelemer at 0, 27.2, 54.3, or 162.9 mg/kg twice daily (4 dogs per sex in each group) for 9 days. All dogs survived to study termination.

Clinical observations related to CANALEVIA-CA1 included discolored red feces, watery feces, and vomiting in a dose-dependent manner with increased incidence in the higher dose groups.

Hematology findings related to CANALEVIA-CA1 included 3 dogs that had a decreased hematocrit (reference range 37.2-52%) at study end compared to acclimation: 1 male administered 27.2 mg/kg with hematocrit of 39.6% prior to dosing and 35.8% on Day 9; 1 female administered 162.9 mg/kg with hematocrit of 40.7% prior to dosing and 36.4% on Day 9; and 1 female administered 162.9 mg/kg with hematocrit of 36.4% prior to dosing and 36.1% on Day 9.

There were no clinically relevant or significant findings for body weight, physical examination, food consumption, electrocardiogram, ophthalmoscopic, or necropsy examinations.

Target Animal Toxicity Studies: In two separate laboratory studies, healthy six to seven month old Beagle dogs were orally administered crofelemer (not commercial formulation) at 0, 50, 175, or 600 mg/kg once daily (four dogs per sex in each group) for 30 days and nine months duration, respectively. All dogs survived to study termination.

Clinical observations related to crofelemer included abnormal feces (mainly black and rust colored mucoid feces and diarrhea) observed as soon as 1 day after the first administration and occurred in a dosedependent manner with increased incidence in the higher dose groups. Dogs in the 600 mg/kg/day group did not gain weight at the same rate, had decreased food consumption, and higher incidences of vomiting compared to the other groups.

Hematology findings related to crofelemer at the dose of 600 mg/kg/day were consistent with a microcytic, hypochromic anemia with mild regeneration, and thrombocytosis as characterized by decreases in hemoglobin, hematocrit, mean corpuscular volume, mean corpuscular hemoglobin, and mean corpuscular hemoglobin concentration; and increases in platelets, percent reticulocytes, and absolute reticulocytes compared to the other groups. Females at 175 mg/kg/day and males and females at 600 mg/kg/day had increased neutrophils compared to the other groups. Crofelemer-related serum chemistry findings at 600 mg/kg/day, and to a lesser severity at 175 mg/kg/day, included decreased albumin, total protein, cholesterol, calcium, and sodium and increased potassium compared to the other groups.

On necropsy, gross lesions related to crofelemer included localized irritation of the gastrointestinal tract (reddened areas, erosion, and red streaks) and discoloration of the gastrointestinal tract (dark red areas and gray areas) and lymph nodes (red, gray, and green). Gross lesions were observed at all crofelemer doses in a dose-dependent manner where higher doses had higher incidences.

On histopathology, crofelemer-related lesions included congestion in the small and large intestines; inflammation and pigmentation of the gastrointestinal tract and pigmentation in the liver; congestion in the mesenteric and suprapharyngeal lymph nodes; histiocytosis, erythrocytosis, basophilic bodies, and pigmentation of the lymph nodes; and splenic macrophage infiltration. Histopathologic lesions occurred in a dose-dependent manner where the higher doses had higher incidences.

Cardiovascular Study: The cardiovascular effects of crofelemer (not commercial formulation) were evaluated in a laboratory study in four healthy one to one and a half years old male Beagle dogs implanted with radiotelemetry devices. Dogs were orally administered crofelemer at 0, 60, 200, and 600 mg/kg one time. Each dog received all treatments with a seven day washout period between treatments. There were no crofelemer-related effects on the cardiovascular parameters (heart rate, blood pressure, electrocardiograms). Clinical observations related to crofelemer included soft, watery, mucoid, or discolored (brown or red) feces in the 200 and 600 mg/kg groups.

STORAGE INFORMATION:

Store at 20°C-25°C (68°F-77°F) with excursions permitted between 15°C-30°C (59°F-86°F).

HOW SUPPLIED:

CANALEVIA-CA1 tablets are available as white, unscored enteric-coated tablets containing 125mg of crofelemer packaged in bottles containing 60 tablets.

Distributed by:

Jaguar Health Inc., San Francisco, CA 94104

Patheon’s commodity number for Package Insert

JAH 111-060 Rev11/21

PRINCIPAL DISPLAY PANEL - 60 tablet bottle

NDC 86149-111-60

Canalevia™-CA1
(crofelemer delayed-release tablets) 125 mg

For oral use in dogs only.

For the treatment of chemotherapy‐induced diarrhea in dogs.

Conditionally approved by FDA pending a full demonstration of effectiveness under application number 141-552.

Caution: Federal law restricts this drug to use by or on the order of a licensed veterinarian. Use only as directed.

It is a violation of Federal law to use this product other than as directed in teh labeling.

Read package insert for full precribing information.

Store at 20°C-25°C (68°F-77°F); excursions permitted between 15°C-30°C (59°F-86°F).

Keep out of reach of children.

JAH 111-060 Rev 11/21

Net contents: 60 tablets